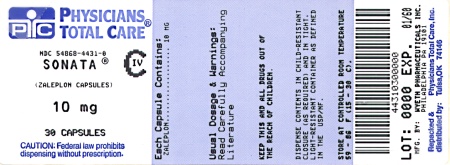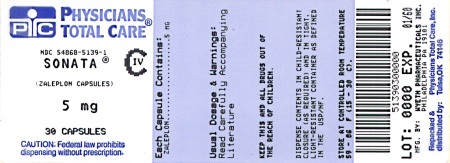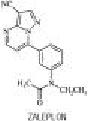 DRUG LABEL: Sonata
NDC: 54868-5139 | Form: CAPSULE
Manufacturer: Physicians Total Care, Inc.
Category: prescription | Type: HUMAN PRESCRIPTION DRUG LABEL
Date: 20100527
DEA Schedule: CIV

ACTIVE INGREDIENTS: ZALEPLON 5 mg/1 1
INACTIVE INGREDIENTS: CELLULOSE, MICROCRYSTALLINE; STARCH, CORN; SILICON DIOXIDE; SODIUM LAURYL SULFATE; MAGNESIUM STEARATE; LACTOSE MONOHYDRATE; GELATIN; TITANIUM DIOXIDE; D&C YELLOW NO. 10; FD&C BLUE NO. 1; FD&C GREEN NO. 3; FD&C YELLOW NO. 5

CIV

RX only

DESCRIPTION

Zaleplon is a nonbenzodiazepine hypnotic from the pyrazolopyrimidine class. The chemical name of zaleplon is N-[3-(3-cyanopyrazolo[1,5-a]pyrimidin-7-yl)phenyl]-N-ethylacetamide. Its empirical formula is C17H15N5O, and its molecular weight is 305.34. The structural formula is shown below.

ZALEPLON

Zaleplon is a white to off-white powder that is practically insoluble in water and sparingly soluble in alcohol or propylene glycol. Its partition coefficient in octanol/water is constant (log PC = 1.23) over the pH range of 1 to 7.

Sonata® capsules contain zaleplon as the active ingredient. Inactive ingredients consist of microcrystalline cellulose, pregelatinized starch, silicon dioxide, sodium lauryl sulfate, magnesium stearate, lactose, gelatin, titanium dioxide, D&C yellow #10, FD&C blue #1, FD&C green #3, and FD&C yellow #5.

CLINICAL PHARMACOLOGY

Pharmacodynamics and Mechanism of Action

While Sonata (zaleplon) is a hypnotic agent with a chemical structure unrelated to benzodiazepines, barbiturates, or other drugs with known hypnotic properties, it interacts with the gamma-aminobutyric acid-benzodiazepine (GABA-BZ) receptor complex. Subunit modulation of the GABA-BZ receptor chloride channel macromolecular complex is hypothesized to be responsible for some of the pharmacological properties of benzodiazepines, which include sedative, anxiolytic, muscle relaxant, and anticonvulsive effects in animal models.

Other nonclinical studies have also shown that zaleplon binds selectively to the brain omega-1 receptor situated on the alpha subunit of the GABAA/chloride ion channel receptor complex and potentiates t-butyl-bicyclophosphorothionate (TBPS) binding. Studies of binding of zaleplon to recombinant GABAA receptors (α1β1γ2 [omega-1] and α2β1γ2 [omega-2]) have shown that zaleplon has a low affinity for these receptors, with preferential binding to the omega-1 receptor.

Pharmacokinetics

The pharmacokinetics of zaleplon have been investigated in more than 500 healthy subjects (young and elderly), nursing mothers, and patients with hepatic disease or renal disease. In healthy subjects, the pharmacokinetic profile has been examined after single doses of up to 60 mg and once-daily administration at 15 mg and 30 mg for 10 days. Zaleplon was rapidly absorbed with a time to peak concentration (tmax) of approximately 1 hour and a terminal-phase elimination half-life (t1/2) of approximately 1 hour. Zaleplon does not accumulate with once-daily administration and its pharmacokinetics are dose proportional in the therapeutic range.

Absorption

Zaleplon is rapidly and almost completely absorbed following oral administration. Peak plasma concentrations are attained within approximately 1 hour after oral administration. Although zaleplon is well absorbed, its absolute bioavailability is approximately 30% because it undergoes significant presystemic metabolism.

Distribution

Zaleplon is a lipophilic compound with a volume of distribution of approximately 1.4 L/kg following intravenous (IV) administration, indicating substantial distribution into extravascular tissues. The in vitro plasma protein binding is approximately 60%±15% and is independent of zaleplon concentration over the range of 10 ng/mL to 1000 ng/mL. This suggests that zaleplon disposition should not be sensitive to alterations in protein binding. The blood to plasma ratio for zaleplon is approximately 1, indicating that zaleplon is uniformly distributed throughout the blood with no extensive distribution into red blood cells.

Metabolism

After oral administration, zaleplon is extensively metabolized, with less than 1% of the dose excreted unchanged in urine. Zaleplon is primarily metabolized by aldehyde oxidase to form 5-oxo-zaleplon. Zaleplon is metabolized to a lesser extent by cytochrome P450 (CYP) 3A4 to form desethylzaleplon, which is quickly converted, presumably by aldehyde oxidase, to 5-oxo-desethylzaleplon. These oxidative metabolites are then converted to glucuronides and eliminated in urine. All of zaleplon's metabolites are pharmacologically inactive.

Elimination

After either oral or IV administration, zaleplon is rapidly eliminated with a mean t1/2 of approximately 1 hour. The oral-dose plasma clearance of zaleplon is about 3 L/h/kg and the IV zaleplon plasma clearance is approximately 1 L/h/kg. Assuming normal hepatic blood flow and negligible renal clearance of zaleplon, the estimated hepatic extraction ratio of zaleplon is approximately 0.7, indicating that zaleplon is subject to high first-pass metabolism.

After administration of a radiolabeled dose of zaleplon, 70% of the administered dose is recovered in urine within 48 hours (71% recovered within 6 days), almost all as zaleplon metabolites and their glucuronides. An additional 17% is recovered in feces within 6 days, most as 5-oxo-zaleplon.

Effect of Food

In healthy adults a high-fat/heavy meal prolonged the absorption of zaleplon compared to the fasted state, delaying tmax by approximately 2 hours and reducing Cmax by approximately 35%. Zaleplon AUC and elimination half-life were not significantly affected. These results suggest that the effects of Sonata on sleep onset may be reduced if it is taken with or immediately after a high-fat/heavy meal.

Special Populations

Age: The pharmacokinetics of Sonata (zaleplon) have been investigated in three studies with elderly men and women ranging in age from 65 to 85 years. The pharmacokinetics of Sonata in elderly subjects, including those over 75 years of age, are not significantly different from those in young healthy subjects.

Gender: There is no significant difference in the pharmacokinetics of Sonata in men and women.

Race: The pharmacokinetics of zaleplon have been studied in Japanese subjects as representative of Asian populations. For this group, Cmax and AUC were increased 37% and 64%, respectively. This finding can likely be attributed to differences in body weight, or alternatively, may represent differences in enzyme activities resulting from differences in diet, environment, or other factors. The effects of race on pharmacokinetic characteristics in other ethnic groups have not been well characterized.

Hepatic impairment: Zaleplon is metabolized primarily by the liver and undergoes significant presystemic metabolism. Consequently, the oral clearance of zaleplon was reduced by 70% and 87% in compensated and decompensated cirrhotic patients, respectively, leading to marked increases in mean Cmax and AUC (up to 4-fold and 7-fold in compensated and decompensated patients, respectively), in comparison with healthy subjects. The dose of Sonata should therefore be reduced in patients with mild to moderate hepatic impairment (see DOSAGE AND ADMINISTRATION). Sonata is not recommended for use in patients with severe hepatic impairment.

Renal impairment: Because renal excretion of unchanged zaleplon accounts for less than 1% of the administered dose, the pharmacokinetics of zaleplon are not altered in patients with renal insufficiency. No dose adjustment is necessary in patients with mild to moderate renal impairment. Sonata has not been adequately studied in patients with severe renal impairment.

Drug-Drug Interactions

Because zaleplon is primarily metabolized by aldehyde oxidase, and to a lesser extent by CYP3A4, inhibitors of these enzymes might be expected to decrease zaleplon's clearance and inducers of these enzymes might be expected to increase its clearance. Zaleplon has been shown to have minimal effects on the kinetics of warfarin (both R- and S- forms), imipramine, ethanol, ibuprofen, diphenhydramine, thioridazine, and digoxin. However, the effects of zaleplon on inhibition of enzymes involved in the metabolism of other drugs have not been studied. (See Drug Interactions under PRECAUTIONS.)

Clinical Trials Controlled Trials Supporting Effectiveness

Sonata (typically administered in doses of 5 mg, 10 mg, or 20 mg) has been studied in patients with chronic insomnia (n = 3,435) in 12 placebo- and active-drug-controlled trials. Three of the trials were in elderly patients (n = 1,019). It has also been studied in transient insomnia (n = 264). Because of its very short half-life, studies focused on decreasing sleep latency, with less attention to duration of sleep and number of awakenings, for which consistent differences from placebo were not demonstrated. Studies were also carried out to examine the time course of effects on memory and psychomotor function, and to examine withdrawal phenomena.

Transient Insomnia

Normal adults experiencing transient insomnia during the first night in a sleep laboratory were evaluated in a double-blind, parallel-group trial comparing the effects of two doses of Sonata (5 mg and 10 mg) with placebo. Sonata 10 mg, but not 5 mg, was superior to placebo in decreasing latency to persistent sleep (LPS), a polysomnographic measure of time to onset of sleep.

Chronic Insomnia Non-elderly patients:

Adult outpatients with chronic insomnia were evaluated in three double-blind, parallel-group outpatient studies, one of 2 weeks duration and two of 4 weeks duration, that compared the effects of Sonata at doses of 5 mg (in two studies), 10 mg, and 20 mg with placebo on a subjective measure of time to sleep onset (TSO). Sonata 10 mg and 20 mg were consistently superior to placebo for TSO, generally for the full duration of all three studies. Although both doses were effective, the effect was greater and more consistent for the 20-mg dose. The 5-mg dose was less consistently effective than were the 10-mg and 20-mg doses. Sleep latency with Sonata 10 mg and 20 mg was on the order of 10-20 minutes (15%-30%) less than with placebo in these studies.

Adult outpatients with chronic insomnia were evaluated in six double-blind, parallel-group sleep laboratory studies that varied in duration from a single night up to 35 nights. Overall, these studies demonstrated a superiority of Sonata 10 mg and 20 mg over placebo in reducing LPS on the first 2 nights of treatment. At later time points in 5-, 14-, and 28-night studies, a reduction in LPS from baseline was observed for all treatment groups, including the placebo group, and thus, a significant difference between Sonata and placebo was not seen beyond 2 nights. In a 35-night study, Sonata 10 mg was significantly more effective than placebo in reducing LPS at the primary efficacy endpoint on nights 29 and 30.

Elderly patients:

Elderly outpatients with chronic insomnia were evaluated in two 2-week, double-blind, parallel-group outpatient studies that compared the effects of Sonata 5 mg and 10 mg with placebo on a subjective measure of time to sleep onset (TSO). Sonata at both doses was superior to placebo on TSO, generally for the full duration of both studies, with an effect size generally similar to that seen in younger persons. The 10-mg dose tended to have a greater effect in reducing TSO.

Elderly outpatients with chronic insomnia were also evaluated in a 2-night sleep laboratory study involving doses of 5 mg and 10 mg. Both 5-mg and 10-mg doses of Sonata were superior to placebo in reducing latency to persistent sleep (LPS).

Generally in these studies, there was a slight increase in sleep duration, compared to baseline, for all treatment groups, including placebo, and thus, a significant difference from placebo on sleep duration was not demonstrated.

Studies Pertinent to Safety Concerns for Sedative/Hypnotic Drugs Memory Impairment

Studies involving the exposure of normal subjects to single fixed doses of Sonata (10 mg or 20 mg) with structured assessments of short-term memory at fixed times after dosing (eg, 1, 2, 3, 4, 5, 8, and 10 hours) generally revealed the expected impairment of short-term memory at 1 hour, the time of peak exposure to zaleplon, for both doses, with a tendency for the effect to be greater after 20 mg. Consistent with the rapid clearance of zaleplon, memory impairment was no longer present as early as 2 hours post dosing in one study, and in none of the studies after 3-4 hours. Nevertheless, spontaneous reporting of adverse events in larger premarketing clinical trials revealed a difference between Sonata and placebo in the risk of next-day amnesia (3% vs 1%), and an apparent dose-dependency for this event (see ADVERSE REACTIONS).

Sedative/Psychomotor Effects

Studies involving the exposure of normal subjects to single fixed doses of Sonata (zaleplon) (10 mg or 20 mg) with structured assessments of sedation and psychomotor function (eg, reaction time and subjective ratings of alertness) at fixed times after dosing (eg, 1, 2, 3, 4, 5, 8, and 10 hours) generally revealed the expected sedation and impairment of psychomotor function at 1 hour, the time of peak exposure to zaleplon, for both doses. Consistent with the rapid clearance of zaleplon, impairment of psychomotor function was no longer present as early as 2 hours post dosing in one study, and in none of the studies after 3-4 hours. Spontaneous reporting of adverse events in larger premarketing clinical trials did not suggest a difference between Sonata and placebo in the risk of next-day somnolence (see ADVERSE REACTIONS).

Withdrawal-Emergent Anxiety and Insomnia

During nightly use for an extended period, pharmacodynamic tolerance or adaptation to some effects of hypnotics may develop. If the drug has a short elimination half-life, it is possible that a relative deficiency of the drug or its active metabolites (ie, in relationship to the receptor site) may occur at some point in the interval between each night's use. This sequence of events is believed to be responsible for two clinical findings reported to occur after several weeks of nightly use of other rapidly eliminated hypnotics: increased wakefulness during the last quarter of the night and the appearance of increased signs of daytime anxiety.

Zaleplon has a short half-life and no active metabolites. At the primary efficacy endpoint (nights 29 and 30) in a 35-night sleep laboratory study, polysomnographic recordings showed that wakefulness was not significantly longer with Sonata than with placebo during the last quarter of the night. No increase in the signs of daytime anxiety was observed in clinical trials with Sonata. In two sleep laboratory studies involving 14- and 28-nightly doses of Sonata (5 mg and 10 mg in one study and 10 mg and 20 mg in the second) and structured assessments of daytime anxiety, no increases in daytime anxiety were detected. Similarly, in a pooled analysis (all the parallel-group, placebo-controlled studies) of spontaneously reported daytime anxiety, no difference was observed between Sonata and placebo.

Rebound insomnia, defined as a dose-dependent temporary worsening in sleep parameters (latency, total sleep time, and number of awakenings) compared to baseline following discontinuation of treatment, is observed with short- and intermediate-acting hypnotics. Rebound insomnia following discontinuation of Sonata relative to baseline was examined at both nights 1 and 2 following discontinuation in three sleep laboratory studies (14, 28, and 35 nights) and five outpatient studies utilizing patient diaries (14 and 28 nights). Overall, the data suggest that rebound insomnia may be dose dependent. At 20 mg, there appeared to be both objective (polysomnographic) and subjective (diary) evidence of rebound insomnia on the first night after discontinuation of treatment with Sonata. At 5 mg and 10 mg, there was no objectiveand minimal subjective evidence of rebound insomnia on the first night after discontinuation of treatment with Sonata. At all doses, the rebound effect appeared to resolve by the second night following withdrawal. In the 35-night study, there was a worsening in sleep on the first night off for both the 10-mg and 20-mg groups compared to placebo, but not to baseline. This discontinuation-emergent effect was mild, had the characteristics of the return of the symptoms of chronic insomnia, and appeared to resolve by the second night after zaleplon discontinuation.

Other Withdrawal-Emergent Phenomena

The potential for other withdrawal phenomena was also assessed in 14- to 28-night studies, including both the sleep laboratory studies and the outpatient studies, and in open-label studies of 6- and 12-month durations. The Benzodiazepine Withdrawal Symptom Questionnaire was used in several of these studies, both at baseline and then during days 1 and 2 following discontinuation. Withdrawal was operationally defined as the emergence of 3 or more new symptoms after discontinuation. Sonata was not distinguishable from placebo at doses of 5 mg, 10 mg, or 20 mg on this measure, nor was Sonata distinguishable from placebo on spontaneously reported withdrawal-emergent adverse events. There were no instances of withdrawal delirium, withdrawal associated hallucinations, or any other manifestations of severe sedative/hypnotic withdrawal.

INDICATIONS AND USAGE

Sonata is indicated for the short-term treatment of insomnia. Sonata has been shown to decrease the time to sleep onset for up to 30 days in controlled clinical studies (see Clinical Trials under CLINICAL PHARMACOLOGY). It has not been shown to increase total sleep time or decrease the number of awakenings.

The clinical trials performed in support of efficacy ranged from a single night to 5 weeks in duration. The final formal assessments of sleep latency were performed at the end of treatment.

CONTRAINDICATIONS

Hypersensitivity to zaleplon or any excipients in the formulation (see also PRECAUTIONS).

WARNINGS

Because sleep disturbances may be the presenting manifestation of a physical and/or psychiatric disorder, symptomatic treatment of insomnia should be initiated only after a careful evaluation of the patient. The failure of insomnia to remit after 7 to 10 days of treatment may indicate the presence of a primary psychiatric and/or medical illness that should be evaluated. Worsening of insomnia or the emergence of new thinking or behavior abnormalities may be the consequence of an unrecognized psychiatric or physical disorder. Such findings have emerged during the course of treatment with sedative/hypnotic drugs, including Sonata. Because some of the important adverse effects of Sonata appear to be dose-related, it is important to use the lowest possible effective dose, especially in the elderly (see DOSAGE AND ADMINISTRATION).

A variety of abnormal thinking and behavior changes have been reported to occur in association with the use of sedative/hypnotics. Some of these changes may be characterized by decreased inhibition (eg, aggressiveness and extroversion that seem out of character), similar to effects produced by alcohol and other CNS depressants. Other reported behavioral changes have included bizarre behavior, agitation, hallucinations, and depersonalization. Amnesia and other neuropsychiatric symptoms may occur unpredictably. In primarily depressed patients, worsening of depression, including suicidal thinking, has been reported in association with the use of sedative/hypnotics.

It can rarely be determined with certainty whether a particular instance of the abnormal behaviors listed above is drug induced, spontaneous in origin, or a result of an underlying psychiatric or physical disorder. Nonetheless, the emergence of any new behavioral sign or symptom of concern requires careful and immediate evaluation.

Following rapid dose decrease or abrupt discontinuation of the use of sedative/hypnotics, there have been reports of signs and symptoms similar to those associated with withdrawal from other CNS-depressant drugs (see DRUG ABUSE AND DEPENDENCE).

Sonata, like other hypnotics, has CNS-depressant effects. Because of the rapid onset of action, Sonata should only be ingested immediately prior to going to bed or after the patient has gone to bed and has experienced difficulty falling asleep. Patients receiving Sonata should be cautioned against engaging in hazardous occupations requiring complete mental alertness or motor coordination (eg, operating machinery or driving a motor vehicle) after ingesting the drug, including potential impairment of the performance of such activities that may occur the day following ingestion of Sonata. Sonata, as well as other hypnotics, may produce additive CNS-depressant effects when coadministered with other psychotropic medications, anticonvulsants, antihistamines, narcotic analgesics, anesthetics, ethanol, and other drugs that themselves produce CNS depression. Sonata should not be taken with alcohol. Dosage adjustment may be necessary when Sonata is administered with other CNS-depressant agents because of the potentially additive effects.

PRECAUTIONS

General Timing of Drug Administration

Sonata should be taken immediately before bedtime or after the patient has gone to bed and has experienced difficulty falling asleep. As with all sedative/hypnotics, taking Sonata while still up and about may result in short-term memory impairment, hallucinations, impaired coordination, dizziness, and lightheadedness.

Use in the elderly and/or debilitated patients

Impaired motor and/or cognitive performance after repeated exposure or unusual sensitivity to sedative/hypnotic drugs is a concern in the treatment of elderly and/or debilitated patients. A dose of 5 mg is recommended for elderly patients to decrease the possibility of side effects (see DOSAGE AND ADMINISTRATION). Elderly and/or debilitated patients should be monitored closely.

Use in patients with concomitant illness

Clinical experience with Sonata in patients with concomitant systemic illness is limited. Sonata should be used with caution in patients with diseases or conditions that could affect metabolism or hemodynamic responses.

Although preliminary studies did not reveal respiratory depressant effects at hypnotic doses of Sonata in normal subjects, caution should be observed if Sonata (zaleplon) is prescribed to patients with compromised respiratory function, because sedative/hypnotics have the capacity to depress respiratory drive. Controlled trials of acute administration of Sonata 10 mg in patients with mild to moderate chronic obstructive pulmonary disease or moderate obstructive sleep apnea showed no evidence of alterations in blood gases or apnea/hypopnea index, respectively. However, patients with compromised respiration due to preexisting illness should be monitored carefully.

The dose of Sonata should be reduced to 5 mg in patients with mild to moderate hepatic impairment (see DOSAGE AND ADMINISTRATION). It is not recommended for use in patients with severe hepatic impairment.

No dose adjustment is necessary in patients with mild to moderate renal impairment. Sonata has not been adequately studied in patients with severe renal impairment.

Use in patients with depression

As with other sedative/hypnotic drugs, Sonata should be administered with caution to patients exhibiting signs or symptoms of depression. Suicidal tendencies may be present in such patients and protective measures may be required. Intentional overdosage is more common in this group of patients (see OVERDOSAGE); therefore, the least amount of drug that is feasible should be prescribed for the patient at any one time.

This product contains FD&C Yellow No. 5 (tartrazine) which may cause allergic-type reactions (including bronchial asthma) in certain susceptible persons. Although the overall incidence of FD&C Yellow No. 5 (tartrazine) sensitivity in the general population is low, it is frequently seen in patients who also have aspirin hypersensitivity.

Information for Patients

Patient information is printed at the end of this insert. To assure safe and effective use of Sonata, the information and instructions provided in the patient information section should be discussed with patients.

Laboratory Tests

There are no specific laboratory tests recommended.

Drug Interactions

As with all drugs, the potential exists for interaction with other drugs by a variety of mechanisms.

CNS-Active Drugs

Ethanol: Sonata 10 mg potentiated the CNS-impairing effects of ethanol 0.75 g/kg on balance testing and reaction time for 1 hour after ethanol administration and on the digit symbol substitution test (DSST), symbol copying test, and the variability component of the divided attention test for 2.5 hours after ethanol administration. The potentiation resulted from a CNS pharmacodynamic interaction; zaleplon did not affect the pharmacokinetics of ethanol.

Imipramine: Coadministration of single doses of Sonata 20 mg and imipramine 75 mg produced additive effects on decreased alertness and impaired psychomotor performance for 2 to 4 hours after administration. The interaction was pharmacodynamic with no alteration of the pharmacokinetics of either drug.

Paroxetine: Coadministration of a single dose of Sonata 20 mg and paroxetine 20 mg daily for 7 days did not produce any interaction on psychomotor performance. Additionally, paroxetine did not alter the pharmacokinetics of Sonata, reflecting the absence of a role of CYP2D6 in zaleplon's metabolism.

Thioridazine: Coadministration of single doses of Sonata 20 mg and thioridazine 50 mg produced additive effects on decreased alertness and impaired psychomotor performance for 2 to 4 hours after administration. The interaction was pharmacodynamic with no alteration of the pharmacokinetics of either drug.

Venlafaxine: Coadministration of a single dose of zaleplon 10 mg and multiple doses of venlafaxine ER (extended release) 150 mg did not result in any significant changes in the pharmacokinetics of either zaleplon of venlafaxine. In addition, there was no pharmacodynamic interaction as a result of coadministration of zaleplon and venlafaxine ER.

Promethazine: Coadministration of a single dose of zaleplon and promethazine (10 and 25 mg, respectively) resulted in a 15% decrease in maximal plasma concentrations of zaleplon, but no change in the area under the plasma concentration-time curve. however, the pharmacodynamics of coadministration of zaleplon and promethazine have not been evaluated. Caution should be exercised when these 2 agents are coadministered.

Drugs That Induce CYP3A4

Rifampin: CYP3A4 is ordinarily a minor metabolizing enzyme of zaleplon. Multiple-dose administration of the potent CYP3A4 inducer rifampin (600 mg every 24 hours, q24h, for 14 days), however, reduced zaleplon Cmax and AUC by approximately 80%. The coadministration of a potent CYP3A4 enzyme inducer, although not posing a safety concern, thus could lead to ineffectiveness of zaleplon. An alternative non-CYP3A4 substrate hypnotic agent may be considered in patients taking CYP3A4 inducers such as rifampin, phenytoin, carbamazepine, and phenobarbital.

Drugs That Inhibit CYP3A4

CYP3A4 is a minor metabolic pathway for the elimination of zaleplon because the sum of desethylzaleplon (formed via CYP3A4 in vitro) and its metabolites, 5-oxo-desethylzaleplon and 5-oxo-desethylzaleplon glucuronide, account for only 9% of the urinary recovery of a zaleplon dose. Coadministration of single, oral doses of zaleplon with erythromycin (10 mg and 800 mg respectively), a strong, selective CYP3A4 inhibitor, produced a 34% increase in zaleplon's maximal plasma concentrations and a 20% increase in the area under the plasma concentration-time curve. The magnitude of interaction with multiple doses of erythromycin is unknown. Other strong selective CYP3A4 inhibitors such as ketoconazole can also be expected to increase the exposure of zaleplon. A routine dosage adjustment of zaleplon is not considered necessary.

Drugs That Inhibit Aldehyde Oxidase

The aldehyde oxidase enzyme system is less well studied than the cytochrome P450 enzyme system.

Diphenhydramine: Diphenhydramine is reported to be a weak inhibitor of aldehyde oxidase in rat liver, but its inhibitory effects in human liver are not known. There is no pharmacokinetic interaction between zaleplon and diphenhydramine following the administration of a single dose (10 mg and 50 mg, respectively) of each drug. However, because both of these compounds have CNS effects, an additive pharmacodynamic effect is possible.

Drugs That Inhibit Both Aldehyde Oxidase and CYP3A4

Cimetidine: Cimetidine inhibits both aldehyde oxidase (in vitro) and CYP3A4 (in vitro and in vivo), the primary and secondary enzymes, respectively, responsible for zaleplon metabolism. Concomitant administration of Sonata (10 mg) and cimetidine (800 mg) produced an 85% increase in the mean Cmax and AUC of zaleplon. An initial dose of 5 mg should be given to patients who are concomitantly being treated with cimetidine (see DOSAGE AND ADMINISTRATION).

Drugs Highly Bound to Plasma Protein

Zaleplon is not highly bound to plasma proteins (fraction bound 60%±15%); therefore, the disposition of zaleplon is not expected to be sensitive to alterations in protein binding. In addition, administration of Sonata to a patient taking another drug that is highly protein bound should not cause transient increase in free concentrations of the other drug.

Drugs with a Narrow Therapeutic Index

Digoxin: Sonata (10 mg) did not affect the pharmacokinetic or pharmacodynamic profile of digoxin (0.375 mg q24h for 8 days).

Warfarin: Multiple oral doses of Sonata (20 mg q24h for 13 days) did not affect the pharmacokinetics of warfarin (R+)- or (S-)-enantiomers or the pharmacodynamics (prothrombin time) following a single 25-mg oral dose of warfarin.

Drugs That Alter Renal Excretion

Ibuprofen: Ibuprofen is known to affect renal function and, consequently, alter the renal excretion of other drugs. There was no apparent pharmacokinetic interaction between zaleplon and ibuprofen following single dose administration (10 mg and 600 mg, respectively) of each drug. This was expected because zaleplon is primarily metabolized and renal excretion of unchanged zaleplon accounts for less than 1% of the administered dose.

Carcinogenesis, Mutagenesis, and Impairment of Fertility Carcinogenesis

Lifetime carcinogenicity studies of zaleplon were conducted in mice and rats. Mice received doses of 25 mg/kg/day, 50 mg/kg/day, 100 mg/kg/day, and 200 mg/kg/day in the diet for two years. These doses are equivalent to 6 to 49 times the maximum recommended human dose (MRHD) of 20 mg on a mg/m^2 basis. There was a significant increase in the incidence of hepatocellular adenomas in female mice in the high dose group. Rats received doses of 1 mg/kg/day, 10 mg/kg/day, and 20 mg/kg/day in the diet for two years. These doses are equivalent to 0.5 to 10 times the maximum recommended human dose (MRHD) of 20 mg on a mg/m^2 basis. Zaleplon was not carcinogenic in rats.

Mutagenesis

Zaleplon was clastogenic, both in the presence and absence of metabolic activation, causing structural and numerical aberrations (polyploidy and endoreduplication), when tested for chromosomal aberrations in the in vitro Chinese hamster ovary cell assay. In the in vitro human lymphocyte assay, zaleplon caused numerical, but not structural, aberrations only in the presence of metabolic activation at the highest concentrations tested. In other in vitro assays, zaleplon was not mutagenic in the Ames bacterial gene mutation assay or the Chinese hamster ovary HGPRT gene mutation assay. Zaleplon was not clastogenic in two in vivo assays, the mouse bone marrow micronucleus assay and the rat bone marrow chromosomal aberration assay, and did not cause DNA damage in the rat hepatocyte unscheduled DNA synthesis assay.

Impairment of Fertility

In a fertility and reproductive performance study in rats, mortality and decreased fertility were associated with administration of an oral dose of zaleplon of 100 mg/kg/day to males and females prior to and during mating. This dose is equivalent to 49 times the maximum recommended human dose (MRHD) of 20 mg on a mg/m^2 basis. Follow-up studies indicated that impaired fertility was due to an effect on the female.

Pregnancy: Pregnancy Category C

In embryofetal development studies in rats and rabbits, oral administration of up to 100 mg/kg/day and 50 mg/kg/day, respectively, to pregnant animals throughout organogenesis produced no evidence of teratogenicity. These doses are equivalent to 49 (rat) and 48 (rabbit) times the maximum recommended human dose (MRHD) of 20 mg on a mg/m^2 basis. In rats, pre- and postnatal growth was reduced in the offspring of dams receiving 100 mg/kg/day. This dose was also maternally toxic, as evidenced by clinical signs and decreased maternal body weight gain during gestation. The no-effect dose for rat offspring growth reduction was 10 mg/kg (a dose equivalent to 5 times the MRHD of 20 mg on a mg/m^2 basis). No adverse effects on embryofetal development were observed in rabbits at the doses examined.

In a pre- and postnatal development study in rats, increased stillbirth and postnatal mortality, and decreased growth and physical development, were observed in the offspring of females treated with doses of 7 mg/kg/day or greater during the latter part of gestation and throughout lactation. There was no evidence of maternal toxicity at this dose. The no-effect dose for offspring development was 1 mg/kg/day (a dose equivalent to 0.5 times the MRHD of 20 mg on a mg/m^2 basis). When the adverse effects on offspring viability and growth were examined in a cross-fostering study, they appeared to result from both in utero and lactational exposure to the drug.

There are no studies of zaleplon in pregnant women; therefore, Sonata® (zaleplon)is not recommended for use in women during pregnancy.

Labor and Delivery

Sonata has no established use in labor and delivery.

Nursing Mothers

A study in lactating mothers indicated that the clearance and half-life of zaleplon is similar to that in young normal subjects. A small amount of zaleplon is excreted in breast milk, with the highest excreted amount occurring during a feeding at approximately 1 hour after Sonata administration. Since the small amount of the drug from breast milk may result in potentially important concentrations in infants, and because the effects of zaleplon on a nursing infant are not known, it is recommended that nursing mothers not take Sonata.

Pediatric Use

The safety and effectiveness of Sonata in pediatric patients have not been established.

Geriatric Use

A total of 628 patients in double-blind, placebo-controlled, parallel-group clinical trials who received Sonata were at least 65 years of age; of these, 311 received 5 mg and 317 received 10 mg. In both sleep laboratory and outpatient studies, elderly patients with insomnia responded to a 5 mg dose with a reduced sleep latency, and thus 5 mg is the recommended dose in this population. During short-term treatment (14 night studies) of elderly patients with Sonata, no adverse event with a frequency of at least 1% occurred at a significantly higher rate with either 5 mg or 10 mg Sonata than with placebo.

ADVERSE REACTIONS

The premarketing development program for Sonata included zaleplon exposures in patients and/or normal subjects from 2 different groups of studies: approximately 900 normal subjects in clinical pharmacology/pharmacokinetic studies; and approximately 2,900 exposures from patients in placebo-controlled clinical effectiveness studies, corresponding to approximately 450 patient exposure years. The conditions and duration of treatment with Sonata varied greatly and included (in overlapping categories) open-label and double-blind phases of studies, inpatients and outpatients, and short-term or longer-term exposure. Adverse reactions were assessed by collecting adverse events, results of physical examinations, vital signs, weights, laboratory analyses, and ECGs.

Adverse events during exposure were obtained primarily by general inquiry and recorded by clinical investigators using terminology of their own choosing. Consequently, it is not possible to provide a meaningful estimate of the proportion of individuals experiencing adverse events without first grouping similar types of events into a smaller number of standardized event categories. In the tables and tabulations that follow, COSTART terminology has been used to classify reported adverse events.

The stated frequencies of adverse events represent the proportion of individuals who experienced, at least once, a treatment-emergent adverse event of the type listed. An event was considered treatment-emergent if it occurred for the first time or worsened while receiving therapy following baseline evaluation.

Adverse Findings Observed in Short-Term, Placebo-Controlled Trials Adverse Events Associated With Discontinuation of Treatment

In premarketing placebo-controlled, parallel-group phase 2 and phase 3 clinical trials, 3.1% of 744 patients who received placebo and 3.7% of 2,149 patients who received Sonata discontinued treatment because of an adverse clinical event. This difference was not statistically significant. No event that resulted in discontinuation occurred at a rate of greater than or equal to 1%.

Adverse Events Occurring at an Incidence of 1% or More Among Sonata 20 mg-Treated Patients

Table 1 enumerates the incidence of treatment-emergent adverse events for a pool of three 28-night and one 35-night placebo-controlled studies of Sonata at doses of 5 mg or 10 mg and 20 mg. The table includes only those events that occurred in 1% or more of patients treated with Sonata 20 mg and that had a higher incidence in patients treated with Sonata 20 mg than in placebo-treated patients.

The prescriber should be aware that these figures cannot be used to predict the incidence of adverse events in the course of usual medical practice where patient characteristics and other factors differ from those which prevailed in the clinical trials. Similarly, the cited frequencies cannot be compared with figures obtained from other clinical investigations involving different treatments, uses, and investigators. The cited figures, however, do provide the prescribing physician with some basis for estimating the relative contribution of drug and non-drug factors to the adverse event incidence rate in the population studied.

Table 1 Incidence (%) of Treatment-Emergent Adverse Events in Long-Term (28 and 35 Nights) Placebo-Controlled Clinical Trials of Sonata^1
Body System | Placebo | Sonata 5 mg or 10 mg | Sonata 20 mg
Preferred Term | (n = 344) | (n = 569) | (n = 297)
Body as a whole
Abdominal pain | 3 | 6 | 6
Asthenia | 5 | 5 | 7
Headache | 35 | 30 | 42
Malaise | less than 1 | less than 1 | 2
Photosensitivity reaction | less than 1 | less than 1 | 1
Digestive system
Anorexia | less than 1 | less than 1 | 2
Colitis | 0 | 0 | 1
Nausea | 7 | 6 | 8
Metabolic and nutritional
Peripheral edema | less than 1 | less than 1 | 1
Nervous system
Amnesia | 1 | 2 | 4
Confusion | less than 1 | less than 1 | 1
Depersonalization | less than 1 | less than 1 | 2
Dizziness | 7 | 7 | 9
Hallucinations | less than 1 | less than 1 | 1
Hypertonia | less than 1 | 1 | 1
Hypesthesia | less than 1 | less than 1 | 2
Paresthesia | 1 | 3 | 3
Somnolence | 4 | 5 | 6
Tremor | 1 | 2 | 2
Vertigo | less than 1 | less than 1 | 1
Respiratory system
Epistaxis | less than 1 | less than 1 | 1
Special senses
Abnormal vision | less than 1 | less than 1 | 2
Ear pain | 0 | less than 1 | 1
Eye pain | 2 | 4 | 3
Hyperacusis | less than 1 | 1 | 2
Parosmia | less than 1 | less than 1 | 2
Urogenital system
Dysmenorrhea | 2 | 3 | 4

1: Events for which the incidence for Sonata 20 mg-treated patients was at least 1% and greater than the incidence among placebo-treated patients. Incidence greater than 1% has been rounded to the nearest whole number. Other Adverse Events Observed During the Premarketing Evaluation of Sonata

Listed below are COSTART terms that reflect treatment-emergent adverse events as defined in the introduction to the ADVERSE REACTIONS section. These events were reported by patients treated with Sonata (zaleplon) at doses in a range of 5 mg/day to 20 mg/day during premarketing phase 2 and phase 3 clinical trials throughout the United States, Canada, and Europe, including approximately 2,900 patients. All reported events are included except those already listed in Table 1 or elsewhere in labeling, those events for which a drug cause was remote, and those event terms that were so general as to be uninformative. It is important to emphasize that although the events reported occurred during treatment with Sonata, they were not necessarily caused by it.

Events are further categorized by body system and listed in order of decreasing frequency according to the following definitions: frequent adverse events are those occurring on one or more occasions in at least 1/100 patients; infrequent adverse events are those occurring in less than 1/100 patients but at least 1/1,000 patients; rare events are those occurring in fewer than 1/1,000 patients.

Body as a whole - Frequent: back pain, chest pain, fever; Infrequent: chest pain substernal, chills, face edema, generalized edema, hangover effect, neck rigidity.

Cardiovascular system - Frequent: migraine; Infrequent: angina pectoris, bundle branch block, hypertension, hypotension, palpitation, syncope, tachycardia, vasodilatation, ventricular extrasystoles; Rare: bigeminy, cerebral ischemia, cyanosis, pericardial effusion, postural hypotension, pulmonary embolus, sinus bradycardia, thrombophlebitis, ventricular tachycardia.

Digestive system - Frequent: constipation, dry mouth, dyspepsia; Infrequent: eructation, esophagitis, flatulence, gastritis, gastroenteritis, gingivitis, glossitis, increased appetite, melena, mouth ulceration, rectal hemorrhage, stomatitis; Rare: aphthous stomatitis, biliary pain, bruxism, cardiospasm, cheilitis, cholelithiasis, duodenal ulcer, dysphagia, enteritis, gum hemorrhage, increased salivation, intestinal obstruction, abnormal liver function tests, peptic ulcer, tongue discoloration, tongue edema, ulcerative stomatitis.

Endocrine system - Rare: diabetes mellitus, goiter, hypothyroidism.

Hemic and lymphatic system - Infrequent: anemia, ecchymosis, lymphadenopathy; Rare: eosinophilia, leukocytosis, lymphocytosis, purpura.

Metabolic and nutritional - Infrequent: edema, gout, hypercholesteremia, thirst, weight gain; Rare: bilirubinemia, hyperglycemia, hyperuricemia, hypoglycemia, hypoglycemic reaction, ketosis, lactose intolerance, AST (SGOT) increased, ALT (SGPT) increased, weight loss.

Musculoskeletal system - Frequent: arthralgia, arthritis, myalgia; Infrequent: arthrosis, bursitis, joint disorder (mainly swelling, stiffness, and pain), myasthenia, tenosynovitis; Rare: myositis, osteoporosis.

Nervous system - Frequent: anxiety, depression, nervousness, thinking abnormal (mainly difficulty concentrating); Infrequent: abnormal gait, agitation, apathy, ataxia, circumoral paresthesia, emotional lability, euphoria, hyperesthesia, hyperkinesia, hypotonia, incoordination, insomnia, libido decreased, neuralgia, nystagmus; Rare: CNS stimulation, delusions, dysarthria, dystonia, facial paralysis, hostility, hypokinesia, myoclonus, neuropathy, psychomotor retardation, ptosis, reflexes decreased, reflexes increased, sleep talking, sleep walking, slurred speech, stupor, trismus.

Respiratory system - Frequent: bronchitis; Infrequent: asthma, dyspnea, laryngitis, pneumonia, snoring, voice alteration; Rare: apnea, hiccup, hyperventilation, pleural effusion, sputum increased.

Skin and appendages - Frequent: pruritus, rash; Infrequent: acne, alopecia, contact dermatitis, dry skin, eczema, maculopapular rash, skin hypertrophy, sweating, urticaria, vesiculobullous rash; Rare: melanosis, psoriasis, pustular rash, skin discoloration.

Special senses - Frequent: conjunctivitis, taste perversion; Infrequent: diplopia, dry eyes, photophobia, tinnitus, watery eyes; Rare: abnormality of accommodation, blepharitis, cataract specified, corneal erosion, deafness, eye hemorrhage, glaucoma, labyrinthitis, retinal detachment, taste loss, visual field defect.

Urogenital system - Infrequent: bladder pain, breast pain, cystitis, decreased urine stream, dysuria, hematuria, impotence, kidney calculus, kidney pain, menorrhagia, metrorrhagia, urinary frequency, urinary incontinence, urinary urgency, vaginitis; Rare: albuminuria, delayed menstrual period, leukorrhea, menopause, urethritis, urinary retention, vaginal hemorrhage.

Postmarketing Reports

Anaphylactic/anaphylactoid reactions, including severe reactions.

DRUG ABUSE AND DEPENDENCE

Controlled Substance Class

Sonata is classified as a Schedule IV controlled substance by federal regulation.

Abuse, Dependence, and Tolerance

Abuse and addiction are separate and distinct from physical dependence and tolerance. Abuse is characterized by misuse of the drug for non-medical purposes, often in combination with other psychoactive substances. Physical dependence is a state of adaption that is manifested by a specific withdrawal syndrome that can be produced by abrupt cessation, rapid dose reduction, decreasing blood level of the drug and/or administration of an antagonist. Tolerance is a state of adaptation in which exposure to a drug induces changes that result in a diminution of one or more of the drug's effects over time. Tolerance may occur to both the desired and undesired effects of drugs and may develop at different rates for different effects.

Addiction is a primary, chronic, neurobiological disease with genetic, psychosocial, and environmental factors influencing its development and manifestations. It is characterized by behaviors that include one or more of the following: impaired control over drug use, compulsive use, continued use despite harm, and craving. Drug addiction is a treatable disease, utilizing a multidisciplinary approach, but relapse is common.

Abuse

Two studies assessed the abuse liability of Sonata at doses of 25 mg, 50 mg, and 75 mg in subjects with known histories of sedative drug abuse. The results of these studies indicate that Sonata has an abuse potential similar to benzodiazepine and benzodiazepine-like hypnotics.

Dependence

The potential for developing physical dependence on Sonata and a subsequent withdrawal syndrome was assessed in controlled studies of 14-, 28-, and 35-night durations and in open-label studies of 6- and 12-month durations by examining for the emergence of rebound insomnia following drug discontinuation. Some patients (mostly those treated with 20 mg) experienced a mild rebound insomnia on the first night following withdrawal that appeared to be resolved by the second night. The use of the Benzodiazepine Withdrawal Symptom Questionnaire and examination of any other withdrawal-emergent events did not detect any other evidence for a withdrawal syndrome following abrupt discontinuation of Sonata therapy in pre-marketing studies.

However, available data cannot provide a reliable estimate of the incidence of dependence during treatment at recommended doses of Sonata. Other sedative/hypnotics have been associated with various signs and symptoms following abrupt discontinuation, ranging from mild dysphoria and insomnia to a withdrawal syndrome that may include abdominal and muscle cramps, vomiting, sweating, tremors, and convulsions. Seizures have been observed in two patients, one of which had a prior seizure, in clinical trials with Sonata. Seizures and death have been seen following the withdrawal of zaleplon from animals at doses many times higher than those proposed for human use. Because individuals with a history of addiction to, or abuse of, drugs or alcohol are at risk of habituation and dependence, they should be under careful surveillance when receiving Sonata or any other hypnotic.

Tolerance

Possible tolerance to the hypnotic effects of Sonata 10 mg and 20 mg was assessed by evaluating time to sleep onset for Sonata compared with placebo in two 28-night placebo-controlled studies and latency to persistent sleep in one 35-night placebo-controlled study where tolerance was evaluated on nights 29 and 30. No development of tolerance to Sonata was observed for time to sleep onset over 4 weeks.

OVERDOSAGE

There is limited pre-marketing clinical experience with the effects of an overdosage of Sonata. Two cases of overdose were reported. One was the accidental ingestion by a 2½ year old boy of 20 mg to 40 mg of zaleplon. The second was a 20 year old man who took 100 mg zaleplon plus 2.25 mg of triazolam. Both were treated and recovered uneventfully.

Signs and Symptoms

Signs and symptoms of overdose effects of CNS depressants can be expected to present as exaggerations of the pharmacological effects noted in preclinical testing. Overdose is usually manifested by degrees of central nervous system depression ranging from drowsiness to coma. In mild cases, symptoms include drowsiness, mental confusion, and lethargy; in more serious cases, symptoms may include ataxia, hypotonia, hypotension, respiratory depression, rarely coma, and very rarely death.

Recommended Treatment

General symptomatic and supportive measures should be used along with immediate gastric lavage where appropriate. Intravenous fluids should be administered as needed. Animal studies suggest that flumazenil is an antagonist to zaleplon. However, there is no pre-marketing clinical experience with the use of flumazenil as an antidote to a Sonata overdose. As in all cases of drug overdose, respiration, pulse, blood pressure, and other appropriate signs should be monitored and general supportive measures employed. Hypotension and CNS depression should be monitored and treated by appropriate medical intervention.

Poison Control Center

As with the management of all overdosage, the possibility of multiple drug ingestion should be considered. The physician may wish to consider contacting a poison control center for up-to-date information on the management of hypnotic drug product overdosage.

DOSAGE AND ADMINISTRATION

The dose of Sonata should be individualized. The recommended dose of Sonata for most nonelderly adults is 10 mg. For certain low weight individuals, 5 mg may be a sufficient dose. Although the risk of certain adverse events associated with the use of Sonata appears to be dose dependent, the 20 mg dose has been shown to be adequately tolerated and may be considered for the occasional patient who does not benefit from a trial of a lower dose. Doses above 20 mg have not been adequately evaluated and are not recommended.

Sonata should be taken immediately before bedtime or after the patient has gone to bed and has experienced difficulty falling asleep (see PRECAUTIONS.). Taking Sonata with or immediately after a heavy, high-fat meal results in slower absorption and would be expected to reduce the effect of Sonata on sleep latency (see Pharmacokinetics under CLINICAL PHARMACOLOGY).

Special Populations

Elderly patients and debilitated patients appear to be more sensitive to the effects of hypnotics, and respond to 5 mg of Sonata. The recommended dose for these patients is therefore 5 mg. Doses over 10 mg are not recommended.

Hepatic insufficiency: Patients with mild to moderate hepatic impairment should be treated with Sonata 5 mg because clearance is reduced in this population. Sonata is not recommended for use in patients with severe hepatic impairment.

Renal insufficiency: No dose adjustment is necessary in patients with mild to moderate renal impairment. Sonata has not been adequately studied in patients with severe renal impairment.

An initial dose of 5 mg should be given to patients concomitantly taking cimetidine because zaleplon clearance is reduced in this population (see Drug Interactions under PRECAUTIONS).

HOW SUPPLIED

Sonata (zaleplon) capsules are supplied as follows:

5 mg: opaque green cap and opaque pale green body with “5 mg” on the cap and “SONATA” on the body.

NDC 54868-5139-0
NDC 54868-5139-1

Bottles of 10
Bottles of 30

10 mg: opaque green cap and opaque light green body with “10 mg” on the cap and “SONATA” on the body.

NDC 54868-4431-1
NDC 54868-4431-0
NDC 54868-4431-3
NDC 54868-4431-2

Bottles of 10
Bottles of 30
Bottles of 50
Bottles of 100

Sonata® is a registered trademark of Jones Pharma Inc.™, a wholly owned subsidiary of King Pharmaceuticals®, Inc.

STORAGE CONDITIONS

Store at controlled room temperature, 20°C to 25°C (68°F to 77°F).

Dispense in a light-resistant container as defined in the USP.

Repackaging and Relabeling by:
Physicians Total Care, Inc.
Tulsa, OK 74146

INFORMATION FOR PATIENTS TAKING SONATA

Your doctor has prescribed Sonata to help you sleep. The following information is intended to guide you in the safe use of this medicine. It is not meant to take the place of your doctor's instructions. If you have any questions about Sonata capsules, be sure to ask your doctor or pharmacist.

Sonata is used to treat difficulty in falling asleep. Sonata works very quickly and has its effect during the first part of the night, since it is rapidly eliminated by the body. You should take Sonata immediately before going to bed or after you have gone to bed and are having difficulty falling asleep. If your principal sleep difficulty is awakening prematurely after falling asleep, there is no evidence that Sonata will be helpful to you. For Sonata to help you fall asleep you should not take it with or immediately after a high-fat/heavy meal.

Sonata belongs to a group of medicines known as the “hypnotics”, or simply, sleep medicines. There are many different sleep medicines available to help people sleep better. Sleep problems are usually temporary, requiring treatment for only a short time, usually 1 or 2 days up to 1 or 2 weeks. Some people have chronic sleep problems that may require more prolonged use of sleep medicine. However, you should not use these medicines for long periods without talking with your doctor about the risks and benefits of prolonged use.

Who should not take Sonata

Do not take Sonata if you are hypersensitive to its active substance, zaleplon, or to any of its inactive ingredients, including tartrazine (FD&C Yellow No. 5).

This product contains FD&C Yellow No. 5 (tartrazine) which may cause allergic-type reactions (including bronchial asthma) in certain susceptible persons. Although the overall incidence of FD&C Yellow No. 5 (tartrazine) sensitivity in the general population is low, it is frequently seen in patients who also have aspirin hypersensitivity.

Side Effects

All medicines have side effects. The most common side effects of sleep medicines are:

- Drowsiness
- Dizziness
- Lightheadedness
- Difficulty with coordination

These side effects with Sonata occur most often within an hour after taking it, so it is especially important to take it only when you are about to go to bed or are already in bed.

Severe allergic reactions, sometimes with difficulty in breathing and possibly life threatening, have been reported and may require immediate medical care.

Sleep medicines can make you sleepy during the day. How drowsy you feel depends upon how your body reacts to the medicine, which sleep medicine you are taking, and how large a dose your doctor has prescribed. Daytime drowsiness is best avoided by taking the lowest dose possible that will still help you sleep at night. Your doctor will work with you to find the dose of Sonata that is best for you. Sonata generally does not cause next-day sleepiness but a few people have reported this.

To manage these side effects while you are taking this medicine:

- When you first start taking Sonata or any other sleep medicine, until you know whether the medicine will still have some carryover effect in you the next day, use extreme care while doing anything that requires complete alertness, such as driving a car, operating machinery, or piloting an aircraft. - NEVER drink alcohol while you are being treated with Sonata or any sleep medicine. Alcohol can increase the side effects of Sonata or any other sleep medicine. - Do not take any other medicines without asking your doctor first. This includes medicines you can buy without a prescription. Some medicines can cause drowsiness and are best avoided while taking Sonata. - Always take the exact dose of Sonata prescribed by your doctor. Never change your dose without talking to your doctor first.

Special Concerns

There are some special problems that may occur while taking sleep medicines.

Memory Problems

Sleep medicines may cause a special type of memory loss or “amnesia.” When this occurs, a person may not remember what has happened for several hours after taking the medicine. This is usually not a problem since most people fall asleep after taking the medicine. Memory loss can be a problem, however, when sleep medicines are taken while traveling, such as during an airplane flight and the person wakes up before the effect of the medicine is gone. This has been called “traveler's amnesia.” Memory problems are not common while taking Sonata. In most instances memory problems can be avoided if you take Sonata only when you are able to get 4 or more hours of sleep before you need to be active again. Be sure to talk to your doctor if you think you are having memory problems.

Tolerance

When sleep medicines are used every night for more than a few weeks, they may lose their effectiveness to help you sleep. This is known as “tolerance.” Development of tolerance to Sonata has not been observed in outpatient clinical studies of up to 4 weeks in duration; however, it is unknown if the benefits of Sonata in falling asleep more quickly persist beyond 4 weeks. Sleep medicines should, in most cases, be used only for short periods of time, such as 1 or 2 days and generally no longer than 1 or 2 weeks. If your sleep problems continue, consult your doctor, who will determine whether other measures are needed to overcome your sleep problems.

Dependence

Sleep medicines can cause dependence, especially when these medicines are used regularly for longer than a few weeks or at high doses. Some people develop a need to continue taking their medicines. This is known as dependence or “addiction.”

When people develop dependence, they may have difficulty stopping the sleep medicine. If the medicine is suddenly stopped, the body is not able to function normally and unpleasant symptoms (see Withdrawal) may occur. They may find they have to keep taking the medicine either at the prescribed dose or at increasing doses just to avoid withdrawal symptoms.

All people taking sleep medicines have some risk of becoming dependent on the medicine. However, people who have been dependent on alcohol or other drugs in the past may have a higher chance of becoming addicted to sleep medicines. This possibility must be considered before using these medicines for more than a few weeks. If you have been addicted to alcohol or drugs in the past, it is important to tell your doctor before starting Sonata or any sleep medicine.

Withdrawal

Withdrawal symptoms may occur when sleep medicines are stopped suddenly after being used daily for a long time. In some cases, these symptoms can occur even if the medicine has been used for only a week or two. In mild cases, withdrawal symptoms may include unpleasant feelings. In more severe cases, abdominal and muscle cramps, vomiting, sweating, shakiness, and rarely, seizures may occur. These more severe withdrawal symptoms are very uncommon. Although withdrawal symptoms have not been observed in the relatively limited controlled trials experience with Sonata, there is, nevertheless, the risk of such events in association with the use of any sleep medicines.

Another problem that may occur when sleep medicines are stopped is known as “rebound insomnia.” This means that a person may have more trouble sleeping the first few nights after the medicine is stopped than before starting the medicine. If you should experience rebound insomnia, do not get discouraged. This problem usually goes away on its own after 1 or 2 nights.

If you have been taking Sonata or any other sleep medicine for more than 1 or 2 weeks, do not stop taking it on your own. Always follow your doctor's directions.

Changes In Behavior and Thinking

Some people using sleep medicines have experienced unusual changes in their thinking and/or behavior. These effects are not common. However, they have included:

- more outgoing or aggressive behavior than normal - loss of personal identity - confusion - strange behavior - agitation - hallucinations - worsening of depression - suicidal thoughts

How often these effects occur depends on several factors, such as a person's general health, the use of other medicines, and which sleep medicine is being used. Clinical experience with Sonata (zaleplon) suggests that it is uncommonly associated with these behavior changes.

It is also important to realize that it is rarely clear whether these behavior changes are caused by the medicine, an illness, or occur on their own. In fact, sleep problems that do not improve may be due to illnesses that were present before the medicine was used. If you or your family notice any changes in your behavior, or if you have any unusual or disturbing thoughts, call your doctor immediately.

Pregnancy and Breastfeeding

Sleep medicines may cause sedation or other potential effects in the unborn baby when used during the last weeks of pregnancy. Therefore, Sonata is not recommended for use during pregnancy. Be sure to tell your doctor if you are pregnant, if you are planning to become pregnant, or if you become pregnant while taking Sonata.

In addition, a very small amount of Sonata may be present in breast milk after use of the medication. The effects of very small amounts of Sonata on an infant are not known; therefore, as with all other hypnotics, it is recommended that you not take Sonata if you are breastfeeding a baby.

Safe Use of Sleeping Medicines

To ensure the safe and effective use of Sonata or any other sleep medicine, you should observe the following cautions:

1. Sonata is a prescription medicine and should be used ONLY as directed by your doctor. Follow your doctor's instructions about how to take, when to take, and how long to take Sonata.
2. Never use Sonata or any other sleep medicine for longer than directed by your doctor.
3. If you notice any unusual and/or disturbing thoughts or behavior during treatment with Sonata or any other sleep medicine, contact your doctor.
4. Tell your doctor about any medicines you may be taking, including medicines you may buy without a prescription. You should also tell your doctor if you drink alcohol. DO NOT use alcohol while taking Sonata or any other sleep medicine.
5. Do not take Sonata unless you are able to get 4 or more hours of sleep before you must be active again.
6. Do not increase the prescribed dose of Sonata or any other sleep medicine unless instructed by your doctor.
7. When you first start taking Sonata or any other sleep medicine, until you know whether the medicine will still have some carryover effect in you the next day, use extreme care while doing anything that requires complete alertness, such as driving a car, operating machinery, or piloting an aircraft.
8. Be aware that you may have more sleeping problems the first night or two after stopping any sleep medicine.
9. Be sure to tell your doctor if you are pregnant, if you are planning to become pregnant, if you become pregnant, or are breastfeeding a baby while taking Sonata.
10. As with all prescription medicines, never share Sonata or any other sleep medicine with anyone else. Always store Sonata or any other sleep medicine in the original container and out of reach of children.
11. Be sure to tell your physician if you suffer from depression.
12. Sonata works very quickly. You should only take Sonata immediately before going to bed or after you have gone to bed and are having difficulty falling asleep.
13. For Sonata to work best, you should not take Sonata with or immediately after a high-fat/heavy meal.
14. Some people should start with the lowest dose (5 mg) of Sonata; these include the elderly (ie, ages 65 and over) and people with liver disease.

Prescribing Information as of March 2006.

Distributed by: King Pharmaceuticals, Inc., Bristol, TN 37620
Manufactured by: Wyeth Pharmaceuticals Inc., Philadelphia, PA 19101

PRINCIPAL DISPLAY PANEL

Sonata (zaleplon) capsules

5 mg

10 mg